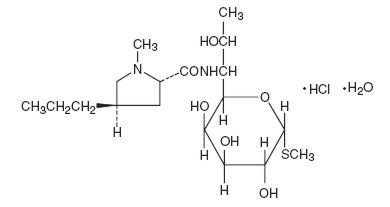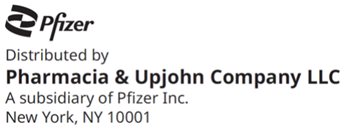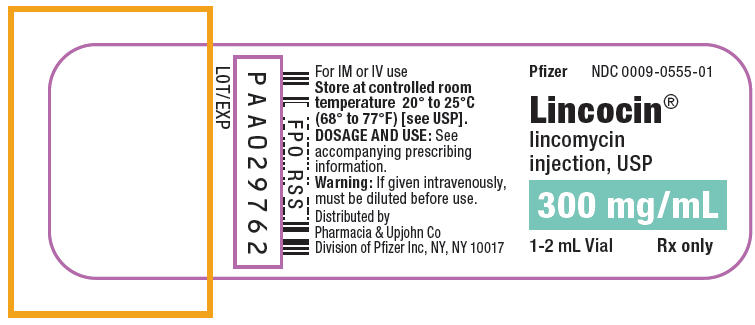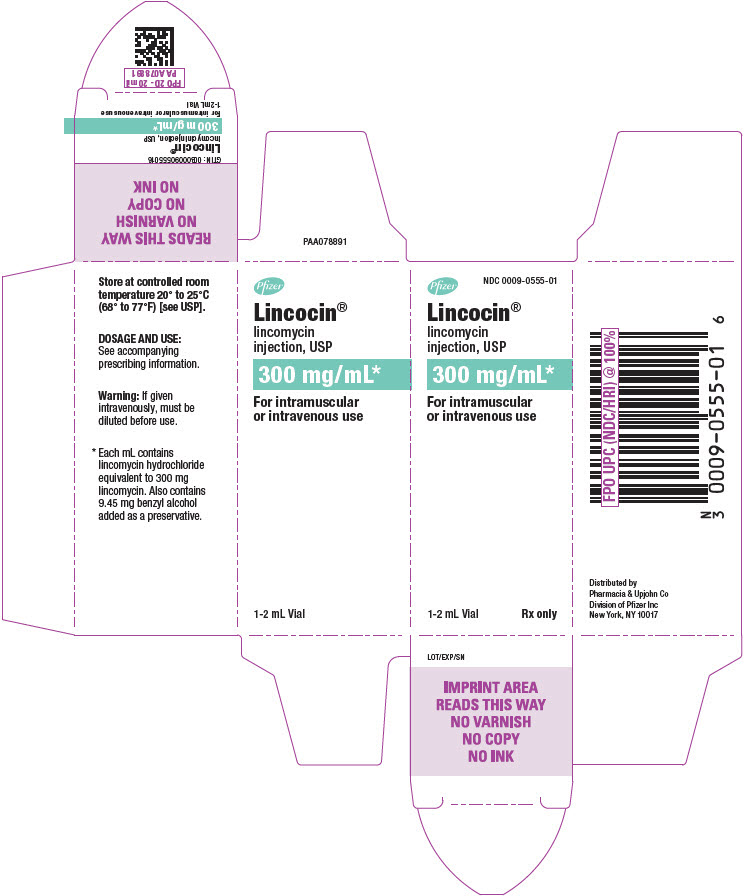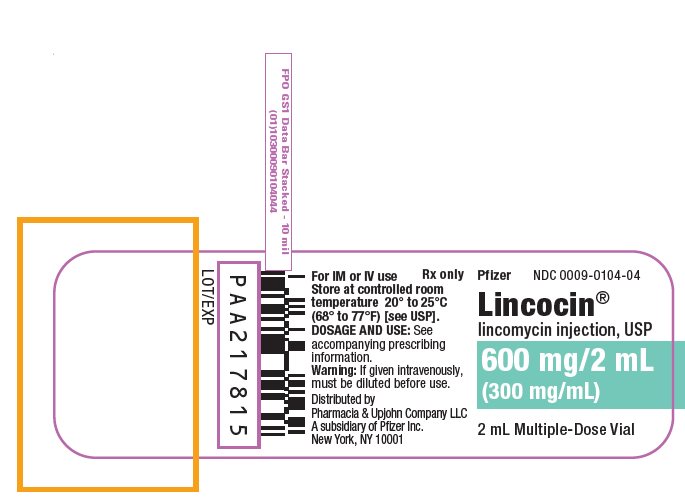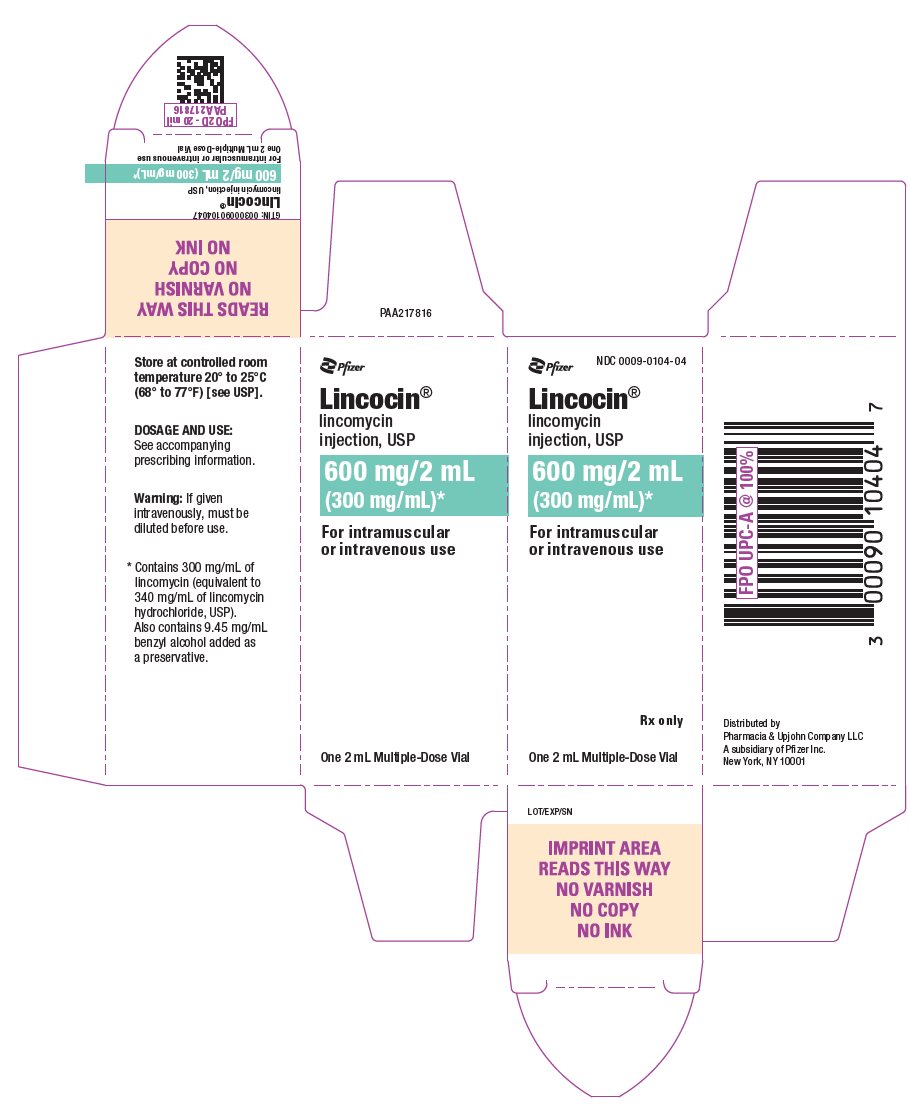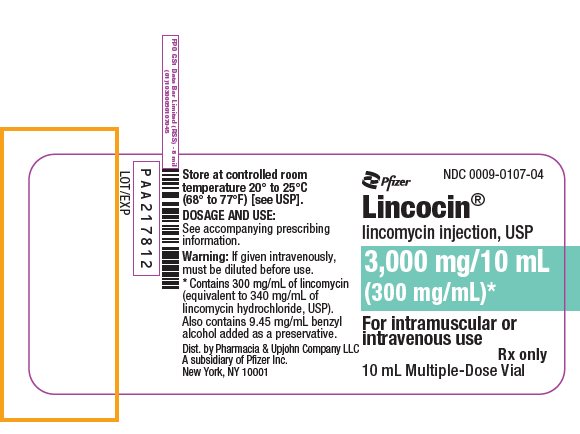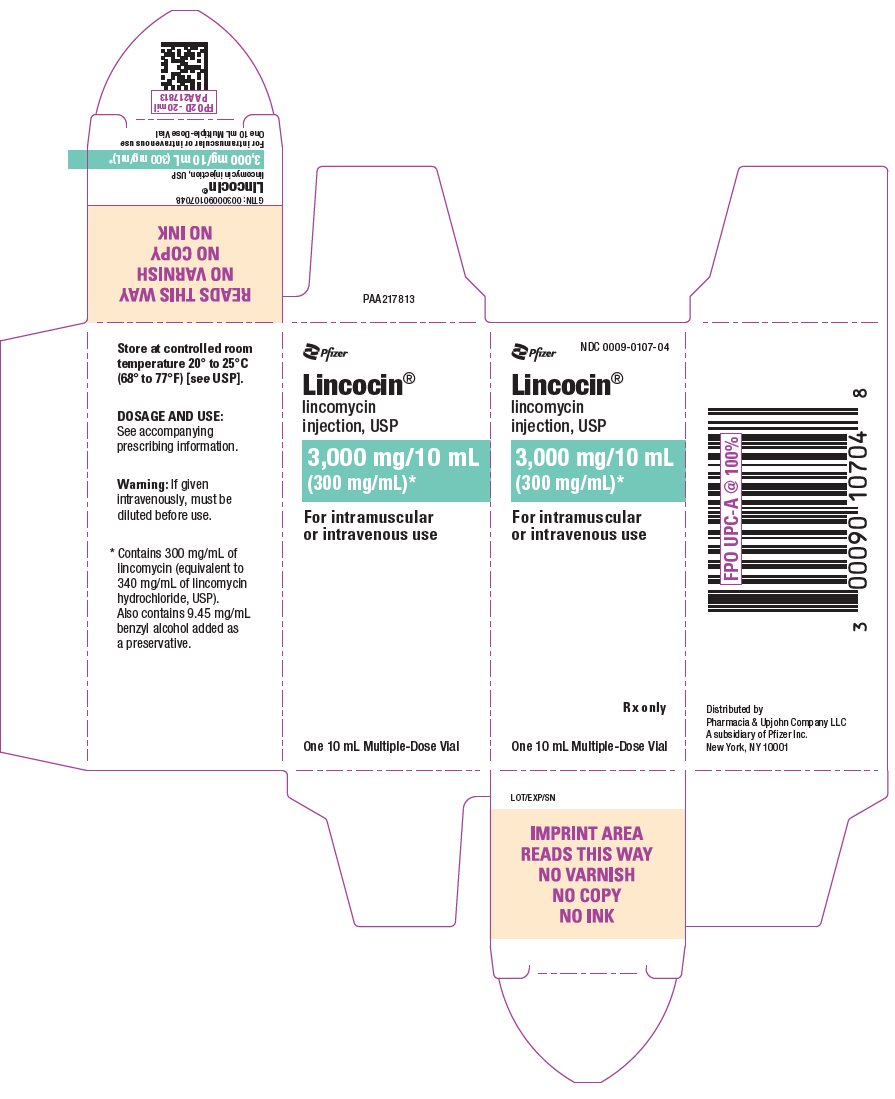 DRUG LABEL: Lincocin
NDC: 0009-0555 | Form: INJECTION, SOLUTION
Manufacturer: Pharmacia & Upjohn Company LLC
Category: prescription | Type: HUMAN PRESCRIPTION DRUG LABEL
Date: 20250310

ACTIVE INGREDIENTS: LINCOMYCIN HYDROCHLORIDE 300 mg/1 mL
INACTIVE INGREDIENTS: BENZYL ALCOHOL 9.45 mg/1 mL

Lincocin®
lincomycin injection, USP

Sterile Solution for Intramuscular and Intravenous Use

To reduce the development of drug-resistant bacteria and maintain the effectiveness of LINCOCIN and other antibacterial drugs, LINCOCIN should be used only to treat or prevent infections that are proven or strongly suspected to be caused by bacteria.

WARNING

Clostridioides difficile associated diarrhea (CDAD) has been reported with use of nearly all antibacterial agents, including LINCOCIN and may range in severity from mild diarrhea to fatal colitis. Treatment with antibacterial agents alters the normal flora of the colon leading to overgrowth of C. difficile.

Because lincomycin therapy has been associated with severe colitis which may end fatally, it should be reserved for serious infections where less toxic antimicrobial agents are inappropriate, as described in the INDICATIONS AND USAGE section. It should not be used in patients with nonbacterial infections such as most upper respiratory tract infections.

C. difficile produces toxins A and B which contribute to the development of CDAD. Hypertoxin producing strains of C. difficile cause increased morbidity and mortality, as these infections can be refractory to antimicrobial therapy and may require colectomy. CDAD must be considered in all patients who present with diarrhea following antibacterial use. Careful medical history is necessary since CDAD has been reported to occur over two months after the administration of antibacterial agents.

If CDAD is suspected or confirmed, ongoing antibacterial use not directed against C. difficile may need to be discontinued. Appropriate fluid and electrolyte management, protein supplementation, antibacterial treatment of C. difficile, and surgical evaluation should be instituted as clinically indicated.

DESCRIPTION

LINCOCIN (lincomycin injection, USP) is a sterile solution containing lincomycin hydrochloride which is the monohydrated salt of lincomycin, a lincosamide antibacterial produced by the growth of a member of the lincolnensis group of Streptomyces lincolnensis (Fam. Streptomycetaceae). The chemical name for lincomycin hydrochloride is Methyl 6,8-dideoxy-6-(1-methyl-trans-4-propyl-L-2-pyrolidinecarboxamido)-1-thio-D-erythro-α-D-galacto-octopyranoside monohydrochloride monohydrate. The molecular formula of lincomycin hydrochloride is C18H34N2O6S.HCl.H2O and the molecular weight is 461.01.

The structural formula is represented below:

Lincomycin hydrochloride is a white or practically white, crystalline powder and is odorless or has a faint odor. Its solutions are acid and are dextrorotatory. Lincomycin hydrochloride is freely soluble in water; soluble in dimethylformamide and very slightly soluble in acetone.

LINCOCIN contains lincomycin hydrochloride in a sterile, clear, colorless solution with benzyl alcohol used as a preservative 9.45 mg/mL, and water for injection.

LINCOCIN is a sterile solution for intramuscular and intravenous use. LINCOCIN is supplied in 2 mL and 10 mL multiple-dose vials containing 300 mg/mL of lincomycin (equivalent to 340 mg/mL of lincomycin hydrochloride, USP).

CLINICAL PHARMACOLOGY

Intramuscular administration of a single dose of 600 mg of lincomycin produces average peak serum concentrations of 11.6 mcg/mL at 60 minutes and maintains therapeutic concentrations for 17 to 20 hours for most susceptible gram-positive organisms. Urinary excretion after this dose ranges from 1.8 to 24.8 percent (mean: 17.3 percent).

A two hour intravenous infusion of 600 mg of lincomycin achieves average peak serum concentrations of 15.9 mcg/mL and maintains therapeutic concentrations for 14 hours for most susceptible gram-positive organisms. Urinary excretion ranges from 4.9 to 30.3 percent (mean: 13.8 percent).

The biological half-life after intramuscular or intravenous administration is 5.4 ± 1.0 hours. The serum half-life of lincomycin may be prolonged in patients with severe renal impairment compared to patients with normal renal function. In patients with hepatic impairment, serum half-life may be twofold longer than in patients with normal hepatic function. Hemodialysis and peritoneal dialysis are not effective in removing lincomycin from the serum.

Tissue distribution studies indicate that bile is an important route of excretion. Significant concentrations have been demonstrated in most body tissues. Although lincomycin appears to diffuse into cerebrospinal fluid (CSF), concentrations of lincomycin in the CSF appear inadequate for the treatment of meningitis.

Microbiology

Mechanism of Action

Lincomycin inhibits bacterial protein synthesis by binding to the 23S RNA of the 50S subunit of the bacterial ribosome. Lincomycin is predominantly bacteriostatic in vitro.

Resistance

Cross resistance has been demonstrated between clindamycin and lincomycin. Resistance is most often due to methylation of specific nucleotides in the 23S RNA of the 50S ribosomal subunit, which can determine cross resistance to macrolides and streptogramins B (MLSB phenotype). Macrolide-resistant isolates of these organisms should be tested for inducible resistance to lincomycin/clindamycin using the D-zone test or other appropriate method.

Antimicrobial Activity

Lincomycin has been shown to be active against most strains of the following bacteria both in vitro and in clinical infections: (see INDICATIONS AND USAGE).
Staphylococcus aureus
Streptococcus pneumoniae

The following in vitro data are available, but their clinical significance is unknown.

Lincomycin has been shown to be active in vitro against the following microorganisms; however, the safety and efficacy of LINCOCIN in treating clinical infections due to these organisms have not been established in adequate and well controlled trials.

Gram-positive bacteria:
Corynebacterium diphtheriae
Streptococcus pyogenes
Viridans group streptococci

Anaerobic bacteria:
Clostridium tetani
Clostridium perfringens

Susceptibility Testing

For specific information regarding susceptibility test interpretive criteria and associated test methods and quality control standards recognized by FDA for this drug, please see: https://www.fda.gov/STIC.

INDICATIONS AND USAGE

LINCOCIN is indicated in the treatment of serious infections due to susceptible strains of streptococci, pneumococci, and staphylococci. Its use should be reserved for penicillin-allergic patients or other patients for whom, in the judgment of the physician, a penicillin is inappropriate. Because of the risk of CDAD, as described in the BOXED WARNING, before selecting lincomycin the physician should consider the nature of the infection and the suitability of other alternatives.

Indicated surgical procedures should be performed in conjunction with antibacterial therapy.

LINCOCIN may be administered concomitantly with other antimicrobial agents when indicated.

LINCOCIN is not indicated in the treatment of minor bacterial infections or viral infections.

To reduce the development of drug-resistant bacteria and maintain the effectiveness of LINCOCIN and other antibacterial drugs, LINCOCIN should be used only to treat or prevent infections that are proven or strongly suspected to be caused by susceptible bacteria. When culture and susceptibility information are available, they should be considered in selecting or modifying antibacterial therapy. In the absence of such data, local epidemiology and susceptibility patterns may contribute to the empiric selection of therapy.

CONTRAINDICATIONS

LINCOCIN is contraindicated in patients previously found to be hypersensitive to lincomycin or clindamycin.

WARNINGS

See BOXED WARNING.

Clostridioides difficile associated diarrhea (CDAD) has been reported with use of nearly all antibacterial agents, including Lincomycin, and may range in severity from mild diarrhea to fatal colitis. Treatment with antibacterial agents alters the normal flora of the colon leading to overgrowth of C. difficile.

C. difficile produces toxins A and B which contribute to the development of CDAD. Hypertoxin producing strains of C. difficile cause increased morbidity and mortality, as these infections can be refractory to antimicrobial therapy and may require colectomy. CDAD must be considered in all patients who present with diarrhea following antibacterial use. Careful medical history is necessary since CDAD has been reported to occur over two months after the administration of antibacterial agents.

If CDAD is suspected or confirmed, ongoing antibacterial use not directed against C. difficile may need to be discontinued. Appropriate fluid and electrolyte management, protein supplementation, antibacterial treatment of C. difficile, and surgical evaluation should be instituted as clinically indicated.

Hypersensitivity

Severe hypersensitivity reactions, including anaphylactic reactions and severe cutaneous adverse reactions (SCAR) such as Stevens-Johnson syndrome (SJS), toxic epidermal necrolysis (TEN), acute generalized exanthematous pustulosis (AGEP), and erythema multiforme (EM) have been reported in patients receiving LINCOCIN therapy. If an anaphylactic reaction or severe skin reaction occurs, LINCOCIN should be discontinued and appropriate therapy should be initiated. (see ADVERSE REACTIONS)

Benzyl Alcohol Toxicity in Pediatric Patients (Gasping Syndrome)

LINCOCIN contains benzyl alcohol as a preservative.

The preservative benzyl alcohol has been associated with serious adverse events, including the "gasping syndrome", and death in pediatric patients. Although normal therapeutic doses of this product ordinarily deliver amounts of benzyl alcohol that are substantially lower than those reported in association with the "gasping syndrome", the minimum amount of benzyl alcohol at which toxicity may occur is not known. The risk of benzyl alcohol toxicity depends on the quantity administered and the liver and kidneys' capacity to detoxify the chemical. Premature and low-birth weight infants may be more likely to develop toxicity.

Inadequate for Use in Meningitis

Although lincomycin appears to diffuse into cerebrospinal fluid, concentrations of lincomycin in the CSF may be inadequate for the treatment of meningitis.

PRECAUTIONS

General

Review of experience to date suggests that a subgroup of older patients with associated severe illness may tolerate diarrhea less well. When LINCOCIN is indicated in these patients, they should be carefully monitored for change in bowel frequency.

LINCOCIN should be prescribed with caution in individuals with a history of gastrointestinal disease, particularly colitis.

LINCOCIN should be used with caution in patients with a history of asthma or significant allergies.

Certain infections may require incision and drainage or other indicated surgical procedures in addition to antibacterial therapy.

The use of LINCOCIN may result in overgrowth of nonsusceptible organisms, particularly yeasts. Should superinfections occur, appropriate measures should be taken as indicated by the clinical situation. When patients with pre-existing Candida infections require therapy with LINCOCIN, concomitant antifungal treatment should be given.

The serum half-life of lincomycin may be prolonged in patients with severe renal impairment compared to patients with normal renal function. In patients with hepatic impairment, serum half-life may be twofold longer than in patients with normal hepatic function.

Patients with severe renal impairment and/or hepatic impairment should be dosed with caution and serum lincomycin concentrations monitored during high-dose therapy. (see DOSAGE AND ADMINISTRATION)

Lincomycin MUST be diluted prior to intravenous infusion. For intravenous infusion, infuse over at least 60 minutes as directed in the DOSAGE AND ADMINISTRATION Section. Do NOT administer as an intravenous bolus. Severe cardiopulmonary reactions have occurred at greater than the recommended concentration and rate.

Prescribing LINCOCIN in the absence of a proven or strongly suspected bacterial infection or a prophylactic indication is unlikely to provide benefit to the patient and increases the risk of the development of drug-resistant bacteria.

Information for Patients

Patients should be counseled that antibacterial drugs including LINCOCIN should only be used to treat bacterial infections. They do not treat viral infections (e.g., the common cold). When LINCOCIN is prescribed to treat a bacterial infection, patients should be told that although it is common to feel better early in the course of therapy, the medication should be taken exactly as directed. Skipping doses or not completing the full course of therapy may (1) decrease the effectiveness of the immediate treatment and (2) increase the likelihood that bacteria will develop resistance and will not be treatable by LINCOCIN or other antibacterial drugs in the future.

Diarrhea is a common problem caused by antibacterial which usually ends when the antibacterial is discontinued. Sometimes after starting treatment with an antibacterial, patients can develop watery and bloody stools (with or without stomach cramps and fever) even as late as two or more months after taking the last dose of the antibacterial. If this occurs, patients should contact their physician as soon as possible.

Laboratory Tests

During prolonged therapy with LINCOCIN, periodic liver and kidney function tests and blood counts should be performed.

Drug Interactions

Lincomycin has been shown to have neuromuscular blocking properties that may enhance the action of other neuromuscular blocking agents; therefore, it should be used with caution in patients receiving such agents.

Carcinogenesis, Mutagenesis, Impairment of Fertility

The carcinogenic potential of lincomycin has not been evaluated.

Lincomycin was not found to be mutagenic in the Ames Salmonella reversion assay or the V79 Chinese hamster lung cells at the HGPRT locus. It did not induce DNA strand breaks in V79 Chinese hamster lung cells as measured by alkaline elution or chromosomal abnormalities in cultured human lymphocytes. In vivo, lincomycin was negative in both the rat and mouse micronucleus assays and it did not induce sex-linked recessive lethal mutations in the offspring of male Drosophila. However, lincomycin did cause unscheduled DNA syntheses in freshly isolated rat hepatocytes.

Impairment of fertility was not observed in male or female rats given oral 300 mg/kg doses of lincomycin (0.36 times the highest recommended human dose based on mg/m^2).

Pregnancy

There are no adequate and well-controlled studies in pregnant women. LINCOCIN Sterile Solution contains benzyl alcohol as a preservative. Benzyl alcohol can cross the placenta. See WARNINGS. LINCOCIN should be used during pregnancy only if clearly needed.

Teratogenic Effects

In a study with 60 pregnant women, cord serum concentrations were approximately 25% of the maternal serum concentrations, indicating that lincomycin crosses the placenta, and no substantial accumulation occurred in the amniotic fluid. Experience with 345 obstetrical patients receiving LINCOCIN revealed no ill effects related to pregnancy.

There was no evidence of teratogenicity when lincomycin was administered in diet to pregnant Sprague Dawley rats during the period of major organogenesis at doses up to 5000 mg/kg (approximately 6 times the maximum recommended human dose [MRHD], respectively, based on body surface area comparison).

Nonteratogenic Effects

Reproduction studies performed in rats administered oral lincomycin in diet for 2 weeks prior to mating, throughout pregnancy and lactation, revealed no adverse effects on survival of offspring from birth to weaning at doses up to 1000 mg/kg (1.2 times the MRHD based on body surface area comparison) up to 2 generations.

Nursing Mothers

Lincomycin has been reported to appear in human milk in concentrations of 0.5 to 2.4 mcg/mL. Because of the potential for serious adverse reactions in nursing infants from LINCOCIN, a decision should be made whether to discontinue nursing, or to discontinue the drug, taking into account the importance of the drug to the mother.

Pediatric Use

LINCOCIN contains benzyl alcohol as a preservative. Benzyl alcohol has been associated with a fatal "Gasping Syndrome" in premature infants. See WARNINGS. Safety and effectiveness in pediatric patients below the age of one month have not been established. (see DOSAGE AND ADMINISTRATION)

ADVERSE REACTIONS

The following adverse reactions have been reported with the use of lincomycin.

Gastrointestinal disorders

Diarrhea, nausea, vomiting, glossitis, stomatitis, abdominal pain, abdominal discomfort [Event has been reported with intravenous injection.] , anal pruritus

Skin and subcutaneous tissue disorders

Toxic epidermal necrolysis, Stevens-Johnson syndrome, acute generalized exanthematous pustulosis, dermatitis bullous, dermatitis exfoliative, erythema multiforme (see WARNINGS), rash, urticaria, pruritus

Infections and infestations

Vaginal infection, pseudomembranous colitis, Clostridioides difficile colitis (see WARNINGS)

Blood and lymphatic system disorders

Pancytopenia, agranulocytosis, aplastic anemia, leukopenia, neutropenia, thrombocytopenic purpura

Immune system disorders

Anaphylactic reaction (see WARNINGS), angioedema, serum sickness

Hepatobiliary disorders

Jaundice, liver function test abnormal, transaminases increased

Renal and urinary disorders

Renal impairment, oliguria, proteinuria, azotemia

Cardiac disorders

Cardio-respiratory arrest (see DOSAGE AND ADMINISTRATION)

Vascular disorders

Hypotension (see DOSAGE AND ADMINISTRATION), thrombophlebitis

Ear and labyrinth disorders

Vertigo, tinnitus

Neurologic disorders

Headache, dizziness, somnolence

General disorders and administration site conditions

Injection site abscess sterile [Reported with intramuscular injection.] , injection site induration, injection site pain, injection site irritation

OVERDOSAGE

Serum concentrations of lincomycin are not appreciably affected by hemodialysis and peritoneal dialysis.

DOSAGE AND ADMINISTRATION

If significant diarrhea occurs during therapy, LINCOCIN should be discontinued. (see BOXED WARNING)

INTRAMUSCULAR

Adults

Serious infections—600 mg (2 mL) intramuscularly every 24 hours. More severe infections—600 mg (2 mL) intramuscularly every 12 hours or more often.

Pediatric patients over 1 month of age

Serious infections—one intramuscular injection of 10 mg/kg (5 mg/lb) every 24 hours. More severe infections—one intramuscular injection of 10 mg/kg (5 mg/lb) every 12 hours or more often.

INTRAVENOUS

Adults

The intravenous dose will be determined by the severity of the infection. For serious infections doses of 600 mg of lincomycin (2 mL of LINCOCIN) to 1 gram are given every 8 to 12 hours. For more severe infections these doses may have to be increased. In life-threatening situations daily intravenous doses of as much as 8 grams have been given. Intravenous doses are given on the basis of 1 gram of lincomycin diluted in not less than 100 mL of appropriate solution (see PHYSICAL COMPATIBILITIES) and infused over a period of not less than one hour.

Dose | Vol. Diluent | Time
600 mg | 100 mL | 1 hr
1 gram | 100 mL | 1 hr
2 grams | 200 mL | 2 hr
3 grams | 300 mL | 3 hr
4 grams | 400 mL | 4 hr

These doses may be repeated as often as required to the limit of the maximum recommended daily dose of 8 grams of lincomycin.

Pediatric patients over 1 month of age

10 to 20 mg/kg/day (5 to 10 mg/lb/day) depending on the severity of the infection may be infused in divided doses as described above for adults.

NOTE: Severe cardiopulmonary reactions have occurred when LINCOCIN has been given at greater than the recommended concentration and rate (see PRECAUTIONS).

SUBCONJUNCTIVAL INJECTION

0.25 mL (75 mg) injected subconjunctivally will result in ocular fluid concentrations of antibacterial (lasting for at least 5 hours) sufficient for most susceptible pathogens.

Patients with Renal Impairment

When therapy with LINCOCIN is required in individuals with severe renal impairment, an appropriate dose is 25 to 30% of that recommended for patients with normally functioning kidneys (see PRECAUTIONS).

Parenteral drug products should be inspected visually for particulate matter and discoloration prior to administration, whenever solution and container permit.

HOW SUPPLIED

LINCOCIN (lincomycin injection, USP) is available as a sterile, clear, and colorless solution in the following strength and package sizes:

Unit of Sale | Concentration
NDC 0009-0555-01 or NDC 0009-0104-04 | 600 mg/2 mL
2 mL multiple-dose vial | (300 mg/mL)
NDC 0009-0107-04 | 3,000 mg/10 mL
10 mL multiple-dose vial | (300 mg/mL)

Each mL of LINCOCIN contains 300 mg lincomycin (equivalent to 340 mg lincomycin hydrochloride, USP); also benzyl alcohol, 9.45 mg added as preservative.

STORAGE AND HANDLING

Store at controlled room temperature 20° to 25°C (68° to 77°F) [see USP].

ANIMAL PHARMACOLOGY

In vivo experimental animal studies demonstrated the effectiveness of LINCOCIN preparations (lincomycin) in protecting animals infected with Streptococcus viridans,β-hemolytic Streptococcus, Staphylococcus aureus, Streptococcus pneumoniae and Leptospira pomona. It was ineffective in Klebsiella, Pasteurella, Pseudomonas, Salmonella and Shigella infections.

PHYSICAL COMPATIBILITIES

Physically compatible for 24 hours at room temperature unless otherwise indicated.

Infusion Solutions
5% Dextrose Injection
10% Dextrose Injection
5% Dextrose and 0.9% Sodium Chloride Injection
10% Dextrose and 0.9% Sodium Chloride Injection
Ringer's Injection

^1/6 M Sodium Lactate Injection
Travert 10%-Electrolyte No. 1
Dextran in Saline 6% w/v

Vitamins in Infusion Solutions
B-Complex
B-Complex with Ascorbic Acid

Antibacterial in Infusion Solutions
Penicillin G Sodium (Satisfactory for 4 hours)
Cephalothin
Tetracycline HCl
Cephaloridine
Colistimethate (Satisfactory for 4 hours)
Ampicillin
Methicillin
Chloramphenicol
Polymyxin B Sulfate

Physically Incompatible with:
Novobiocin
Kanamycin

IT SHOULD BE EMPHASIZED THAT THE COMPATIBLE AND INCOMPATIBLE DETERMINATIONS ARE PHYSICAL OBSERVATIONS ONLY, NOT CHEMICAL DETERMINATIONS. ADEQUATE CLINICAL EVALUATION OF THE SAFETY AND EFFICACY OF THESE COMBINATIONS HAS NOT BEEN PERFORMED.

Rx only

For medical information about LINCOCIN, please visit www.pfizermedinfo.com or call 1-800-438-1985.

LAB-0138-15.0
Revised October 2023

PRINCIPAL DISPLAY PANEL - 1-2 mL Vial Label

Pfizer

NDC 0009-0555-01

Lincocin®
lincomycin
injection, USP

300 mg/mL

1-2 mL Vial
Rx only

PRINCIPAL DISPLAY PANEL - 2 mL Vial Carton

Pfizer
NDC 0009-0555-01

Lincocin®
lincomycin
injection, USP

300 mg/mL*

For intramuscular
or intravenous use

1-2 mL Vial
Rx only

PRINCIPAL DISPLAY PANEL - 2 mL Vial Label 0009-0104

Pfizer
NDC 0009-0104-04

Lincocin®
lincomycin injection, USP

600 mg/2 mL
(300 mg/mL)

2 mL Multiple-Dose Vial

PRINCIPAL DISPLAY PANEL - 2 mL Vial Carton 0009-0104

Pfizer
NDC 0009-0104-04

Lincocin®
lincomycin
injection, USP

600 mg/2 mL
(300 mg/mL)*

For intramuscular
or intravenous use

Rx only

One 2 mL Multiple-Dose Vial

PRINCIPAL DISPLAY PANEL - 10 mL Vial Label

Pfizer
NDC 0009-0107-04

Lincocin®
lincomycin injection, USP

3,000 mg/10 mL
(300 mg/mL)*

For intramuscular or
intravenous use

Rx only

10 mL Multiple-Dose Vial

PRINCIPAL DISPLAY PANEL - 10 mL Vial Carton

Pfizer
NDC 0009-0107-04

Lincocin®
lincomycin
injection, USP

3,000 mg/10 mL
(300 mg/mL)*

For intramuscular
or intravenous use

Rx only

One 10 mL Multiple-Dose Vial